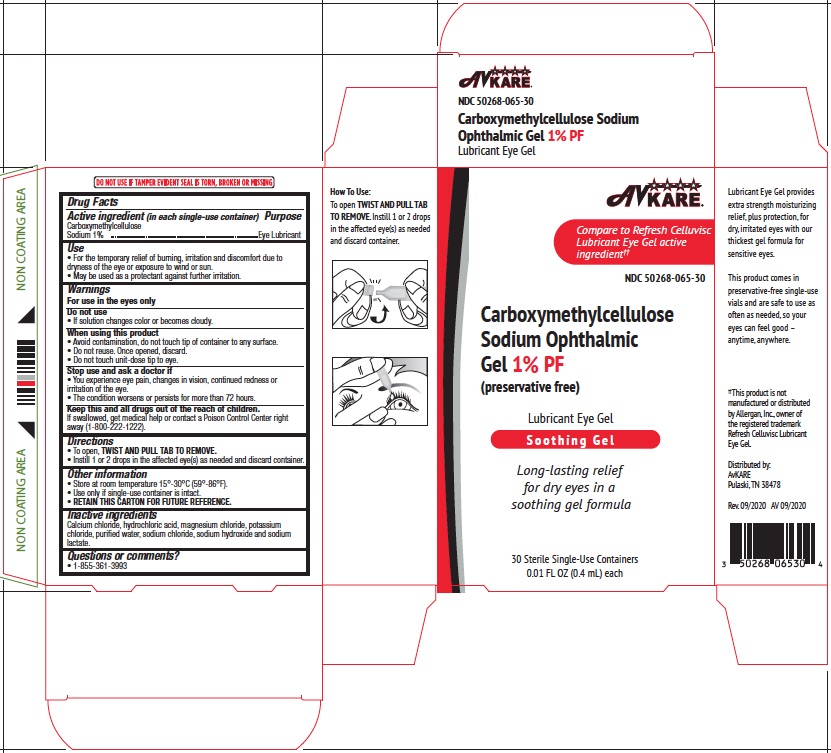 DRUG LABEL: carboxymethylcellulose sodium
NDC: 50268-065 | Form: GEL
Manufacturer: AvPAK
Category: otc | Type: HUMAN OTC DRUG LABEL
Date: 20260108

ACTIVE INGREDIENTS: CARBOXYMETHYLCELLULOSE SODIUM 10 mg/1 mL
INACTIVE INGREDIENTS: MAGNESIUM CHLORIDE; CALCIUM CHLORIDE; POTASSIUM CHLORIDE; WATER; SODIUM CHLORIDE; SODIUM LACTATE; HYDROCHLORIC ACID; SODIUM HYDROXIDE

Carboxymethylcellulose Sodium Ophthalmic Gel !% PF
(preservative free)
Lubricant Eye Gel

Active ingredient

Carboxymethylcellulose sodium 1%

Purpose

Eye lubricant

Uses

- For the temporary relief of burning, irritation, and discomfort due to dryness of the eye or exposure to wind or sun.
- May be used as a protectant against further irritation.

Warnings

- For external use only.
- To avoid contamination, do not touch tip of container to any surface. Do not reuse. Once opened, discard
- Do not touch unit-dose tip to eye.
- If solution changes color or becomes cloudy, do not use.

Stop use and ask a doctor if

you experience eye pain, changes in vision, continued redness or irritation of the eye, or if the condition worsens or persists for more than 72 hours.

Keep out of reach of children.

If swallowed, get medical help or contact a Poison Control Center right away.

Directions

To open, TWIST AND PULL TAB TO REMOVE. Instill 1 or 2 drops in the affected eye(s) as needed and discard container.

Other information

- Use only if single-use container is intact.
- Store at room temperature 15°-30°C (59°-86°F).
- RETAIN THIS CARTON FOR FUTURE REFERENCE.

Inactive ingredients

Calcium chloride, hydrochloric acid, magnesium chloride, potassium chloride, puried water, sodium chloride, sodium hydroxide and sodium lactate.

Questions or comments?

1-855-361-3993